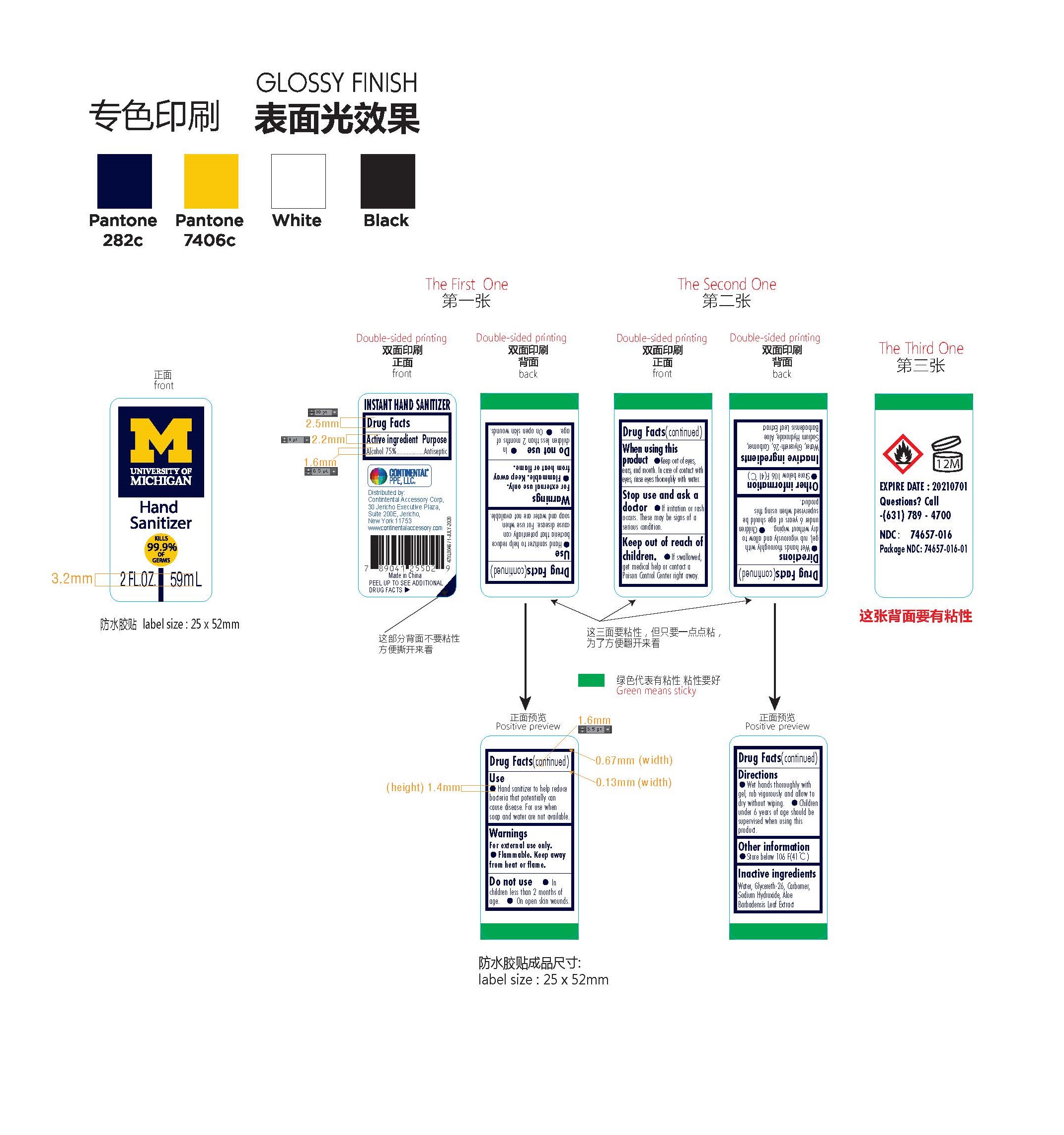 DRUG LABEL: University of Michigan
NDC: 74657-016 | Form: GEL
Manufacturer: Double Body Biotech Limited
Category: otc | Type: HUMAN OTC DRUG LABEL
Date: 20200708

ACTIVE INGREDIENTS: ALCOHOL 75 mL/100 mL
INACTIVE INGREDIENTS: SODIUM HYDROXIDE; GLYCERETH-26; CARBOMER 980; ALOE VERA LEAF; WATER

University of Michigan Hand Sanitizer

Active ingredient

Alcohol 75%

Purpose

Antiseptic

Use

- Hand Sanitizer to help reduce bacteria that potentially can cause disease. For use when soap and water are not available.

Warnings

For external use Only.

- Flammable. Keep away from heat or flame.

Stop use and ask a doctor

- If irritation or rash occurs. These may be signs of a serious condition.

Keep out of reach of children.

- If swallowed, get medical help or contact a Poison Control Center right away.

Do not use

- In children less than 2 months of age.
- On open skin wounds.

Directions

- Wet hands thoroughly with gel, rub vigorously and allow to dry without wiping.
- Children under 6 years of age should be supervised when using this product.

Other information

- Store below 106 F(41℃)

Inactive ingredients

Water, Glycereth-26, Carbomer, Sodium Hydroxide, Aloe Barbadensis Leaf Extract